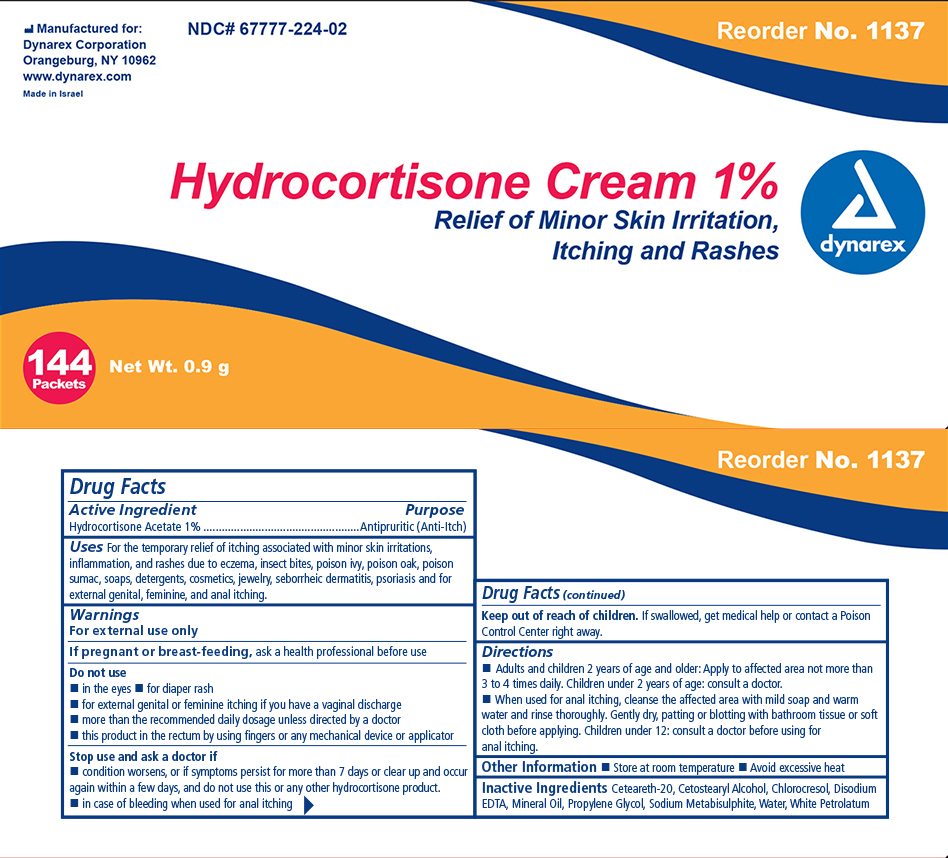 DRUG LABEL: Hydrocortisone
NDC: 67777-224 | Form: CREAM
Manufacturer: Dynarex Corporation
Category: otc | Type: HUMAN OTC DRUG LABEL
Date: 20170405

ACTIVE INGREDIENTS: HYDROCORTISONE ACETATE 1 g/100 g
INACTIVE INGREDIENTS: PROPYLENE GLYCOL; WATER; CETETH-20; CETOSTEARYL ALCOHOL; CHLOROCRESOL; MINERAL OIL; PETROLATUM; SODIUM METABISULFITE; EDETATE DISODIUM

Dynarex Hydrocortisone Cream 1%

Active Ingredient Purpose

Hydrocortisone Acetate 1% Antipruritic (anti-itch)

Warnings:

For external use only

Purpose

Use:

- For the temporary relief of itching associated with minor skin irritations, inflammation, and rashes due to eczema, insect bites, poison ivy, poison oak, poison sumac, soaps, detergents, cosmetics, jewelry, seborrheic dermatitis, psoriasis and for external genital, feminine, and anal itching.

Do not use:

- in the eyes
- for diaper rash
- for external genital or feminine itching if you have a vaginal discharge
- more than the recommended daily dosage unless directed by a doctor
- this product in the rectum by using fingers or any mechanical device or applicator

Stop use and ask a physician if:

- condition worsens, or if symptoms persist for more than 7 days or clear up and occur again within a few days, and do not use this or any other hydrocortisone product.
- in case of bleeding when used for anal itching

Keep out of reach of children

- If swallowed, get medical help or contact a Poison Control Center right away.

Directions:

- Adults and children 2 years of age and older: Apply to affected area not more than 3 to 4 times daily. Children under 2 years of age: consult a doctor.
- When used for anal itching, cleanse the affected area with mild soap and warm water and rinse thoroughly. Gently dry, patting or blotting with bathroom tissue or soft cloth before applying. Children under 12: consult a doctor before using for anal itching.

Other information:

- Store at room temperature
- Avoid excessive heat

Inactive ingredients:

Cetomacrogol 1000, Cetostearyl Alcohol, Chlorocresol, Liquid Paraffin, Propylene Glycol, Purified water, White Soft Paraffin.

INDICATIONS AND USAGE

For the temporary relief of itching associated with minor skin irritations, inflammation, and rashes due to eczema, insect bites, poison ivy, poison oak, poison sumac, soaps, detergents, cosmetics, jewelry, seborrheic dermatitis, psoriasis and for external genital, feminine, and anal itching.

Principal Display Panel

1137 Hydro Cort.jpg